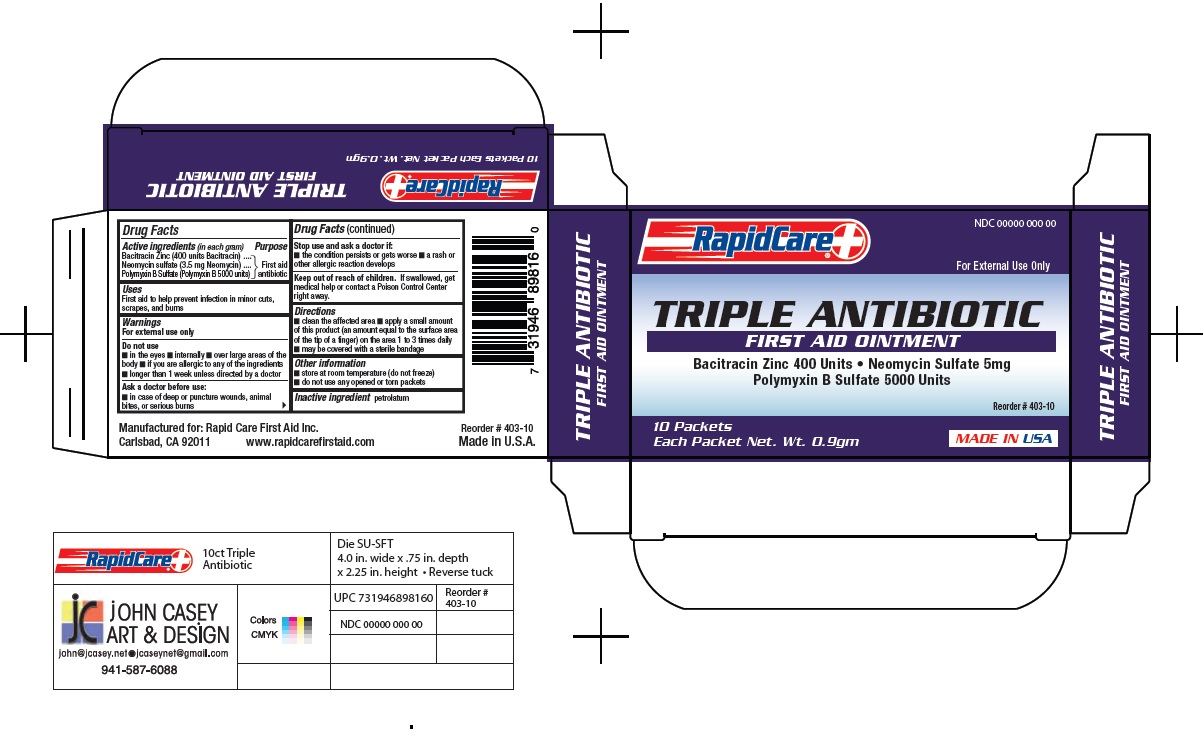 DRUG LABEL: Triple Antibiotic
NDC: 73659-010 | Form: OINTMENT
Manufacturer: Rapid Care, Inc
Category: otc | Type: HUMAN OTC DRUG LABEL
Date: 20211014

ACTIVE INGREDIENTS: POLYMYXIN B SULFATE 5000 [USP'U]/1 g; BACITRACIN ZINC 400 [USP'U]/1 g; NEOMYCIN SULFATE 3.5 mg/1 g
INACTIVE INGREDIENTS: PETROLATUM

RapidCare - Triple Antibiotic- 10 Packet

Active Ingredients

(in each gram)

Bacitracin Zinc (400 units Bacitracin)

Neomycin Sulfate (3.5mg Neomycin)

Polymyxin B Sulfate (Polymyxin B 5000 units)

Purpose

Antibiotics

Uses

First aid to help prevent infection in minor cuts, scrapes or burns

Warnings

For external use only

Do Not Use

- in the eyes
- internally
- over large areas of the body
- if you are allergic to any of the ingredients
- longer than 1 week unless directed by a doctor

Stop use and ask a doctor:

- the condition persists or gets worse
- a rash or other allergic reaction develops

Keep out of reach of children.

If swallowed get medical help or contact a Poison Control right away.

Directions

- clean the affected area
- apply a small amount of this product (an amount equal to the surface area of the tip of a finger) on the area 1 to 3 times daily
- may be covered with a sterile bandage

Inactive ingredient

petrolatum